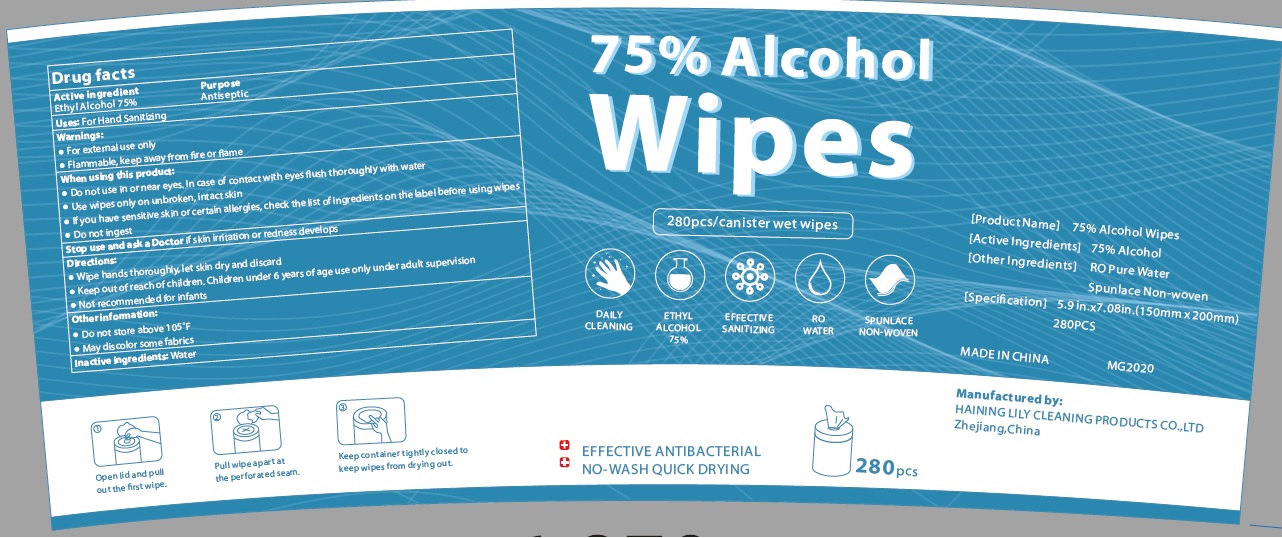 DRUG LABEL: Alcohol Wipes
NDC: 77435-103 | Form: SWAB
Manufacturer: HAINING LILY CLEANING PRODUCTS CO., LTD
Category: otc | Type: HUMAN OTC DRUG LABEL
Date: 20200701

ACTIVE INGREDIENTS: ALCOHOL 75 g/100 g
INACTIVE INGREDIENTS: WATER

alcohol Wipes

Active Ingredient

Alcohol 75%

Purpose

Antiseptic

USE

For hand Sanitizing

KEEP OUT OF REACH OF CHILDREN

Children under 6 year of age use only under adult supervision

Directions

- Wipe hands thoroughly, let skin dry and discard
- Keep out of reach of children, Children under 6 years of age use only under adult supervision.
- Not recommended for infants

Inactive ingredients

Water